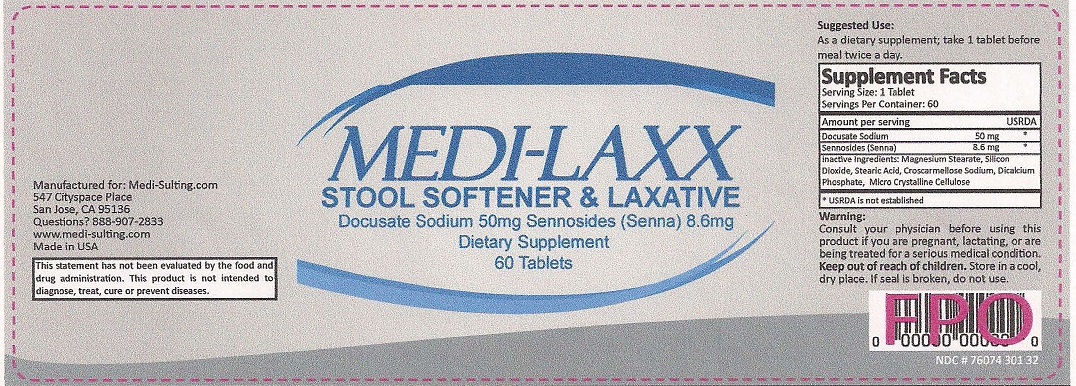 DRUG LABEL: MEDI-LAXX
NDC: 76074-301 | Form: TABLET
Manufacturer: Two Hip Consulting, LLC
Category: other | Type: DIETARY SUPPLEMENT
Date: 20170814

ACTIVE INGREDIENTS: DOCUSATE SODIUM 50 mg/1 1; SENNOSIDES 8.6 mg/1 1
INACTIVE INGREDIENTS: MAGNESIUM STEARATE; SILICON DIOXIDE; STEARIC ACID; CROSCARMELLOSE SODIUM; CALCIUM PHOSPHATE, DIBASIC, ANHYDROUS; CELLULOSE, MICROCRYSTALLINE

HEALTH CLAIM

STOOL SOFTENER AND LAXATVE

PRECAUTIONS

*DO NOT TAKE THIS PRODUCT IF YOU ARE DRIVING OR USING MACHINERY

WARNING:

CONSULT YOUR PHYSICIAN BEFORE USING THIS PRODUCT IF YOU ARE PREGNANT, LACTATING, OR ARE BEING TREATED FOR A SERIOUS MEDICAL CONDITION. KEEP OUT OF REACH OF CHILDREN.

SAFE HANDLING WARNING

STORE IN A COOL, DRY PLACE. IF SEAL IS BROKEN, DO NOT USE.

STATEMENT OF IDENTITY

MEDI-LAXX

STOOL SOFTENER & LAXATIVE

DOCUSATE SODIUM 50MG SENNOSIDES (SENNA) 8.6MG

DIETARY SUPPLEMENT

DOSAGE AND ADMINISTRATION

AMOUNT PER SERVING

DOCUSATE SODIUM 50 MG

SENNOSIDES (SENNA) 8.6 MG

AS A DIETARY SUPPLEMENT, TAKE 1 TABLET BEFORE MEAL TWICE A DAY.